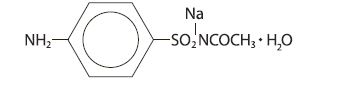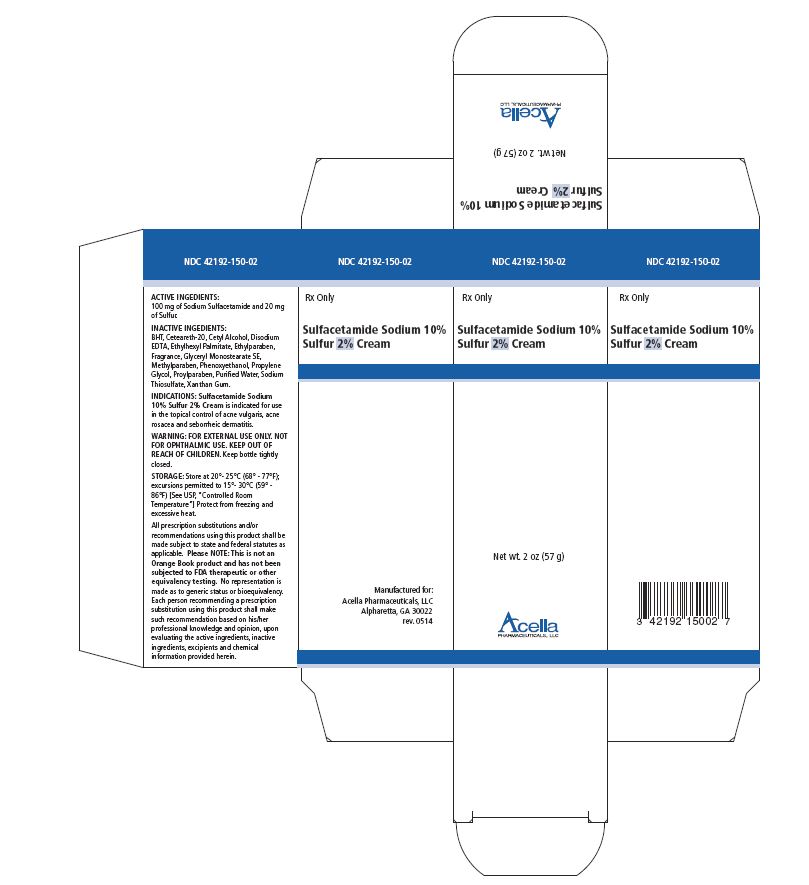 DRUG LABEL: Sodium Sulfacetamide 10 Sulfur 2 cream
NDC: 42192-150 | Form: CREAM
Manufacturer: Acella Pharmaceuticals, LLC
Category: prescription | Type: HUMAN PRESCRIPTION DRUG LABEL
Date: 20250306

ACTIVE INGREDIENTS: SULFACETAMIDE SODIUM 100 mg/1 g; SULFUR 20 mg/1 g
INACTIVE INGREDIENTS: BUTYLATED HYDROXYTOLUENE; POLYOXYL 20 CETOSTEARYL ETHER; CETOSTEARYL ALCOHOL; CETYL ALCOHOL; EDETATE DISODIUM; ETHYLHEXYL PALMITATE; ETHYLPARABEN; GLYCERYL MONOSTEARATE; METHYLPARABEN; PHENOXYETHANOL; PROPYLENE GLYCOL; PROPYLPARABEN; WATER; SODIUM THIOSULFATE; XANTHAN GUM

Sodium Sulfacetamide 10% Sulfur 2% Cream

Rx Only

DESCRIPTION:

Sodium sulfacetamide is a sulfonamide with antibacterial activity while sulfur acts as a keratolytic agent. Chemically sodium sulfacetamide is N-[(4-aminophenyl) sulfonyl]-acetamide, monosodium salt, monohydrate. The structural formula is:

Each gram of Sodium Sulfacetamide 10% Sulfur 2% Cream contains 100 mg of Sodium Sulfacetamide and 20 mg of Sulfur in a base containing BHT, Ceteareth-20, Cetearyl Alcohol, Cetyl Alcohol,Disodium EDTA, Ethylhexyl Palmitate, Ethylparaben, Fragrance, Glyceryl Monostearate SE, Methylparaben, Phenoxyethanol, Propylene Glycol, Propylparaben, Purified Water, Sodium Thiosulfate and Xanthan Gum.

CLINICAL PHARMACOLOGY:

Sodium Sulfacetamide exhibits antibacterial activity. It is believed to block bacterial growth by acting as a competitive antagonist of para-aminobenzoic acid (PABA). While absorption through intact skin has not been determined for sodium sulfacetamide, it is estimated that 1% of topically applied sulfur is absorbed. Although the exact mode of the keralytic activity of sulfur is unknown, it is reported to result from the interaction of sulfur with the cysteine content of keratinocytes. In combination with sulfacetamide, sulfur has been reported to inhibit P. acnes, thereby reducing the associated inflammation.

INDICATIONS:

Sodium Sulfacetamide 10% Sulfur 2% Cream is indicated in the topical control of acne vulgaris, acne rosacea and seborrheic dermatitis.

CONTRAINDICATIONS:

Sodium Sulfacetamide 10% Sulfur 2% Cream is contraindicated for use by patients having known hypersensitivity to sulfonamides, sulfur or any other component of this preparation. Sodium Sulfacetamide 10% Sulfur 2% Cream is not to be used by patients with kidney disease.

WARNINGS:

Although rare, sensitivity to sodium sulfacetamide may occur. Therefore, caution and careful supervision should be observed when prescribing this drug for patients who may be prone to hypersensitivity to topical sulfonamides. Systemic toxic reactions such as agranulocytosis, acute hemolytic anemia, purpura hemorrhagica, drug fever, jaundice and contact dermatitis indicate hypersensitivity to sulfonamides. Particular caution should be employed if areas of denuded or abraded skin are involved.

PRECAUTIONS

GENERAL PRECAUTIONS

FOR EXTERNAL USE ONLY. Keep away from eyes. Keep out of reach of children. Keep container tightly closed.

PRECAUTIONS: General - If irritation develops, use of the product should be discontinued and appropriate therapy instituted. Patients should be carefully observed for possible local irritation or sensitization during long-term therapy. The object of this therapy is to achieve desquamation without irritation, but sodium sulfacetamide and sulfur can cause reddening and scaling of the epidermis. These side effects are not unusual in the treatment of acne vulgaris, but patients should be cautioned about the possibility.

PATIENT COUNSELING INFORMATION

Information for patients - Avoid contact with eyes, eyelids, lips and mucous membranes. If accidental contact occurs, rinse with water. If excessive irritation develops, discontinue use and consult your physician.

CARCINOGENESIS AND MUTAGENESIS AND IMPAIRMENT OF FERTILITY

Carcinogenesis, Mutagenesis and Impairment of Fertility - Long-term studies in animals have not been performed to evaluate carcinogenic potential.

PREGNANCY

Pregnancy: Category C. Animal reproduction studies have not been conducted with Sodium Sulfacetamide 10% Sulfur 2% Cream. It is not known whether Sodium Sulfacetamide 10% Sulfur 2% Cream can cause fetal harm when administered to a pregnant woman or can affect reproduction capacity. Sodium Sulfacetamide 10% Sulfur 2% Cream should be given to a pregnant woman only if clearly needed.

NURSING MOTHERS

NURSING MOTHERS: It is not known whether sodium sulfacetamide is excreted in the human milk following topical use of Sodium Sulfacetamide 10% Sulfur 2% Cream. However, small amounts of orally administered sulfonamides have been reported to be eliminated in human milk. In view of this and because many drugs are excreted in human milk, caution should be exercised when Sodium Sulfacetamide 10% Sulfur 2% Cream is administered to a nursing woman.

PEDIATRIC USE

PEDIATRIC USE: Safety and effectiveness in children under the age of 12 have not been established.

ADVERSE REACTIONS:

Although rare, sodium sulfacetamide may cause local irritation.

DOSAGE AND ADMINISTRATION:

Cleanse skin thoroughly before application. Apply a thin layer to affected areas 1-3 times daily or as directed by a physician. To minimize potential dryness, start with one application daily, then gradually increase to 2-3 times daily as needed or as directed by a physician.

HOW SUPPLIED:

Sodium Sulfacetamide 10% Sulfur 2% Cream is available in 2 oz (57 g) bottles, NDC 42192-150-02.

STORAGE AND HANDLING

Store at 20° - 25°C (68° - 77°F); excursions permitted to 15° - 30°C (59° - 86°F) [see USP Controlled Room Temperature]

KEEP THIS AND ALL MEDICATIONS OUT OF THE REACH OF CHILDREN.

All prescription substitutions using this product shall be made subject to state and federal statutes as applicable. NOTE: this is not an Orange Book product and has not been subjected to FDA therapeutic equivalency or other equivalency testing. No representation is made as to generic status or bioequivalency. Each person recommending a prescription substitution using this product shall make such recommendations based on each such person’s professional opinion and knowledge, upon evaluating the active ingredients, excipients, inactive ingredients and chemical formulation information provided herein.

MANUFACTURED FOR: Acella Pharmaceuticals, LLC
Alpharetta, GA 30022 • 1-800-541-4802

Rev. 0514

PRINCIPAL DISPLAY PANEL - 57 g Bottle Label

NDC 42192-150-02

Rx Only

Sulfacetamide Sodium 10%
Sulfur 2% Cream

Net wt. 2 oz (57 g)

Acella
PHARMACEUTICALS, LLC